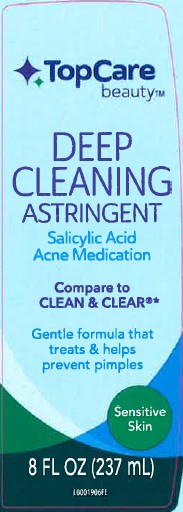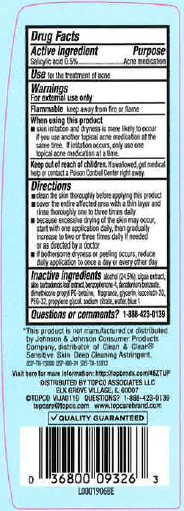 DRUG LABEL: Salicylic Acid
NDC: 36800-875 | Form: LIQUID
Manufacturer: Topco Associates LLC
Category: otc | Type: HUMAN OTC DRUG LABEL
Date: 20260213

ACTIVE INGREDIENTS: SALICYLIC ACID 5 mg/1 mL
INACTIVE INGREDIENTS: ALCOHOL; ALOE; BENZOPHENONE; DENATONIUM BENZOATE; DIMETHICONE; GLYCERIN; ISOCETETH-20; POLYETHYLENE GLYCOL 1500; SODIUM CITRATE; WATER; FD&C BLUE NO. 1

Top Care 875.002/875AD AE
Gentle Astringent

Active ingredient

Salicylic acid 0.5%

Purpose

Acne medication

Use

for the treatment of acne

Warnings

For external use only

Flammable. Keep away from fire or flame.

When using this product

- skin irritation and dryness is more likely to occur if you use another topical acne medication at the same time. If irritation occurs, only use one topical acne medication at a time

Keep out of reach of children.

If swallowed, get medical help or contact a Poison Control Center right away.

Directions

- clean the skin thoroughly before applying this product
- cover the entire affected area with a thin layer and rinse thoroughly one to three times daily
- because excessive drying of the skin may occur, start with one application daily, then gradually increase to two or three times daily if needed or as directed by a doctor
- if bothersome dryness or peeling occurs, reduce daily application to once a day or every other day

Inactive ingredients

alcohol (24.5%), algae extract, aloe barbadensis leaf extract, benzophenone-4, denatonium benzoate, dimethicone propyl PG-betaine, fragrance, glycerin, isoceteth-20, PEG-32, propylene glycol, sodium citrate, water, blue 1

Questions or comments?

1-888-423-0139

ADVERSE REACTION

*This product is not manufactured or distributed by Johnson & Johnson Consumer Products Company, distributor of Clean & Clear®Sensitive Skin Deep Cleaning Astringent.

Visit us here for more information: http://topbrands.com

DISTRIBUTED BY TOPCO ASSOCIATES LLC

150 NORTHEST POINT BOULEVARD

ELK GROVE VILLAGE, IL 60007

1-888-423-0139 TOPCO VIJA0119

topcare@ topco.com

QUALITY GUARANTEED

principal display panel

TopCare

beauty™

DEEP CLEANING

ASTRINGENT

Salicylic Acid

Acne Medication

Compare to CLEAN & CLEAR®*

Gentle formula that treats & helps prevent pimples

Sensitive Skin

8 FL OZ (237 mL)